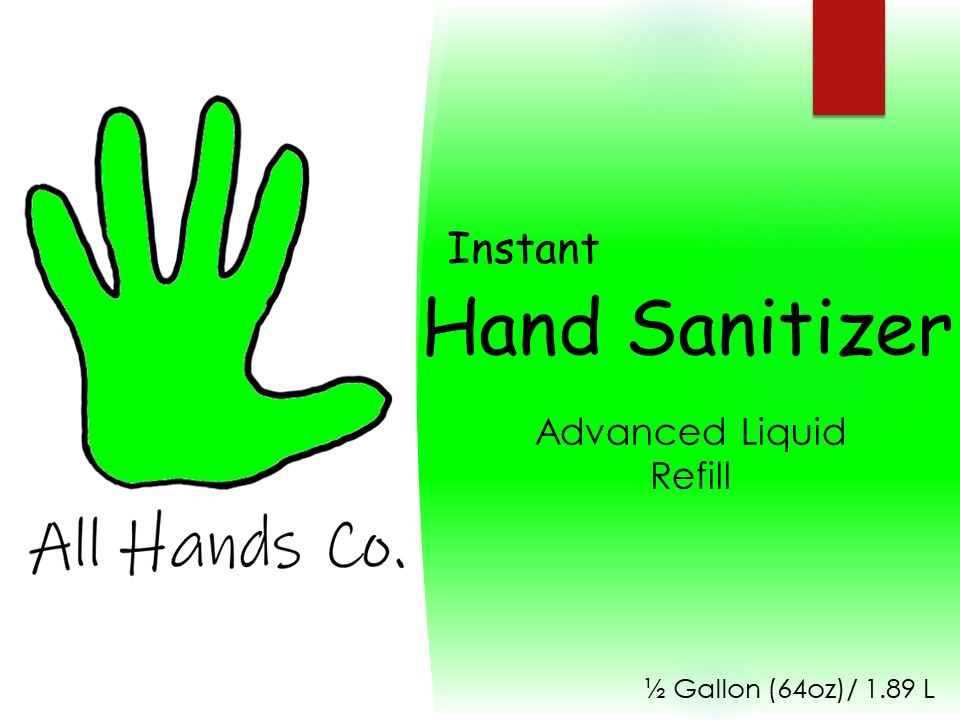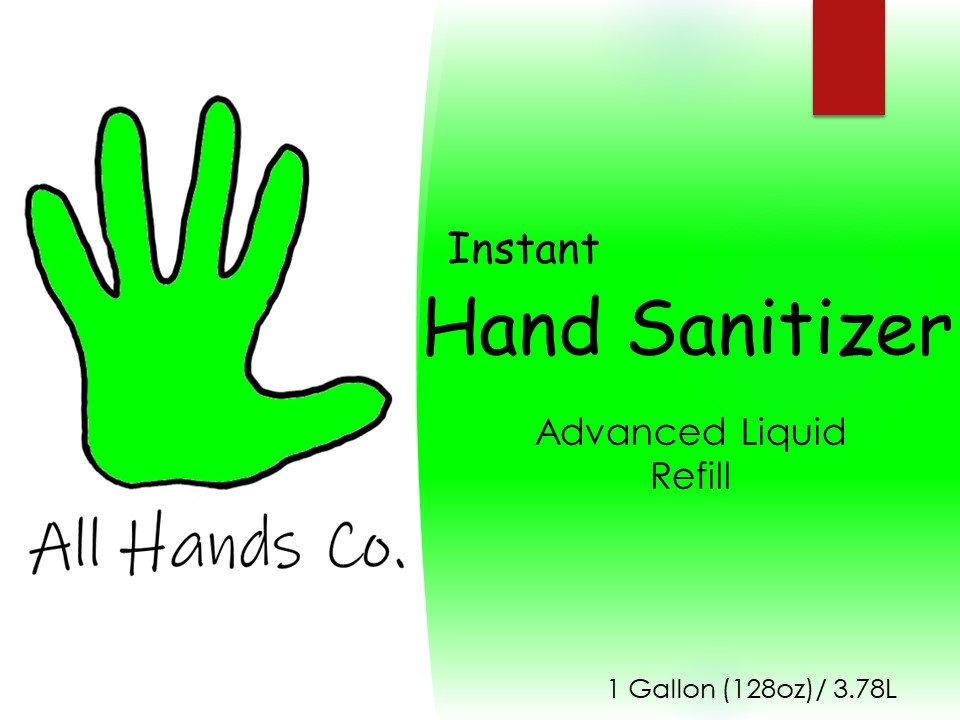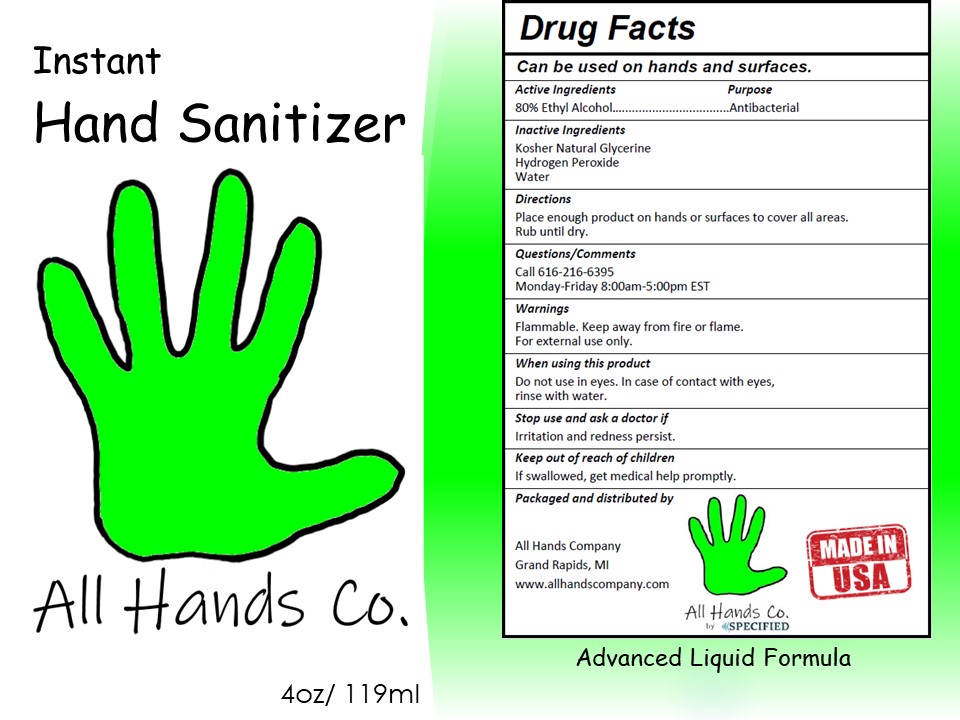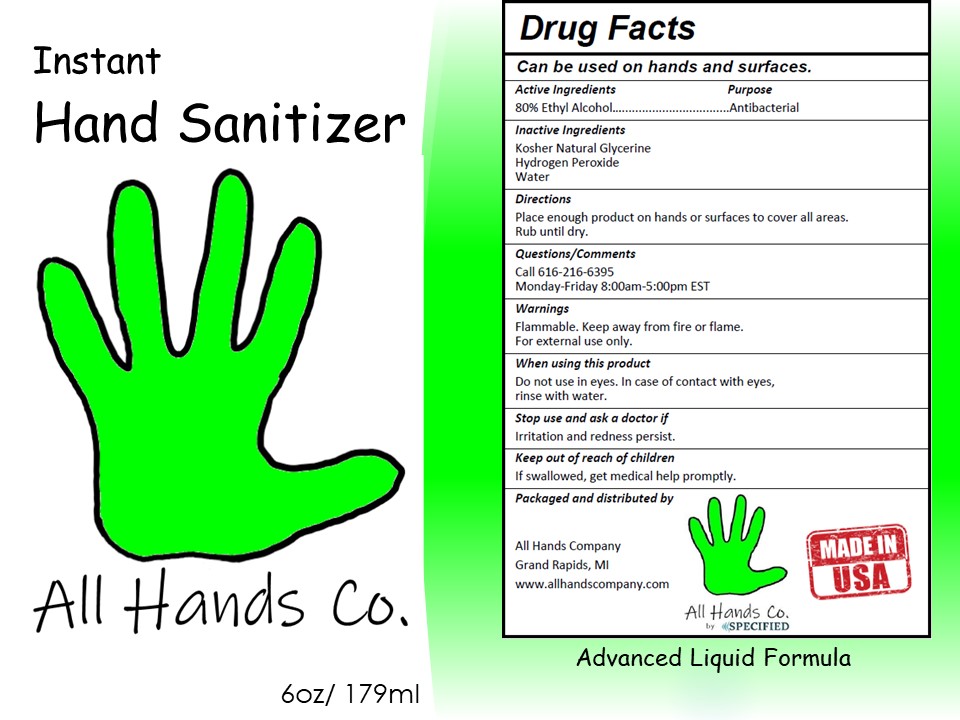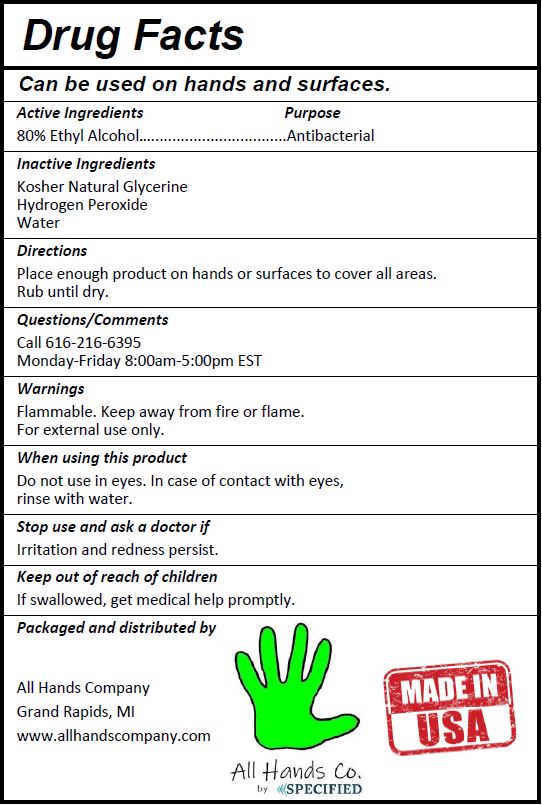 DRUG LABEL: All Hands Co. Hand Sanitizer
NDC: 77163-616 | Form: LIQUID
Manufacturer: Specified Coating Technologies LLC
Category: otc | Type: HUMAN OTC DRUG LABEL
Date: 20200501

ACTIVE INGREDIENTS: ALCOHOL 80 mL/100 mL
INACTIVE INGREDIENTS: GLYCERIN 1.45 mL/100 mL; HYDROGEN PEROXIDE 0.125 mL/100 mL; WATER

This is a hand sanitizer manufactured according to the Temporary Policy for Preparation of Certain Alcohol-Based Hand Sanitizer Products During the Public Health Emergency (CoViD-19); Guidance for Industry.

The hand sanitizer is manufactured using only the following United States Pharmacopoeia (USP) grade ingredients in the preparation of the product (percentage in final product formulation) consistent with World Health Organization (WHO) recommendations:

1. Alcohol (ethanol) (USP or Food Chemical Codex (FCC) grade) (80%, volume/volume (v/v)) in an aqueous solution denatured according to Alcohol and Tobacco Tax and Trade Bureau regulations in 27 CFR part 20.
2. Glycerol (1.45% v/v).
3. Hydrogen peroxide (0.125% v/v).
4. Sterile distilled water or boiled cold water.

The firm does not add other active or inactive ingredients. Different or additional ingredients may impact the quality and potency of the product.

Active Ingredient(s)

Alcohol 80% v/v. Purpose: Antiseptic

Purpose

Antiseptic, Hand Sanitizer

Use

Hand Sanitizer to help reduce bacteria that potentially can cause disease. For use when soap and water are not available.

Warnings

Flammable. Keep away from heat or flame. For external use only.

Do not use

- in children less than 2 months of age
- on open skin wounds

When using this product

Do not use in eyes. In case of contact with eyes, rinse with water.
Stop use and ask a doctor if

Irritation and redness persist.

Stop use and ask a doctor if

Irritation or redness persist.

Keep out of reach of children

If swallowed, get medical help promptly.

Directions

Place enough product on hands to cover all surfaces. Rub until dry.

Other information

- Store between 15-30C (59-86F)
- Avoid freezing and excessive heat above 40C (104F)

Inactive ingredients

Glycerine

Hydrogen Peroxide

Water

Questions/ Comments

Call 616-216-6395

Monday-Friday 8:00am-5:00pm EST

Package Label - Principal Display Panel

4oz 119mL NDC: 77163-616-04 Small Packaging

6oz 179mL NDC: 77163-616-06 Small Packaging

1/2 Gallon 1.89L NDC: 77163-616-64 Small Packaging

1 Gallon 3.78L NDC: 77163-616-01 Small Packaging